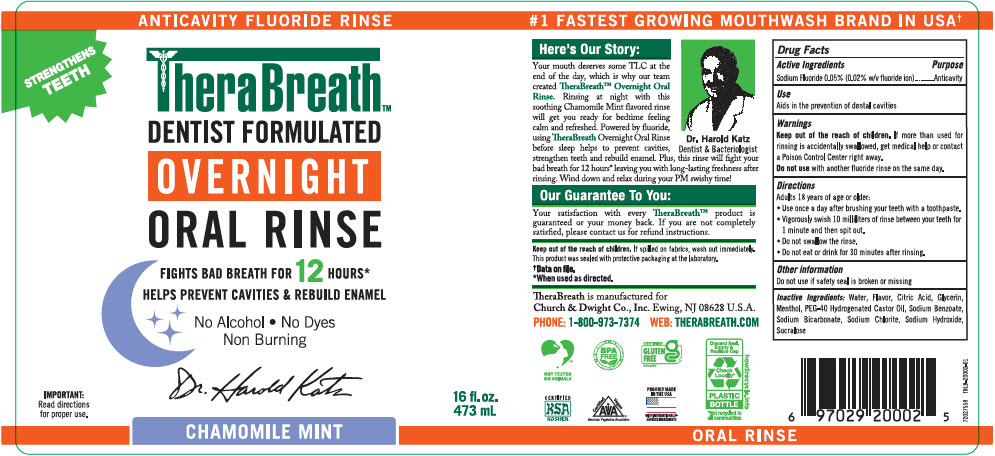 DRUG LABEL: Therabreath Overnight Chamomile Mint
NDC: 10237-262 | Form: RINSE
Manufacturer: Church & Dwight Co., Inc.
Category: otc | Type: HUMAN OTC DRUG LABEL
Date: 20251211

ACTIVE INGREDIENTS: SODIUM FLUORIDE 5 mg/10 mL
INACTIVE INGREDIENTS: WATER; GLYCERIN; SODIUM BENZOATE; SODIUM HYDROXIDE; SODIUM CHLORITE; CITRIC ACID MONOHYDRATE; SUCRALOSE; POLYOXYL 40 HYDROGENATED CASTOR OIL

Therabreath™Overnight Chamomile Mint

Drug Facts

Active Ingredients

Sodium Fluoride 0.05% (0.02% wh fluoride ion)

Purpose

Anticavity

Use

Aids in the prevention of dental cavities

Warnings

KEEP OUT OF REACH OF CHILDREN

Keep out of the reach of children.If more than used for rinsing is accidentally swallowed, gel medical help or contact a Poison Control Center right away.

DO NOT USE

Do not usewith another fluoride rinse on the same day.

Directions

Adults 18 years of age or older:

- Use once a day atter brushing your teeth with a toothpaste.
- Vigorously swish 10 milliliters of rinse between your teeth for 1 minute and then spit out.
- Do not swallow the rinse.
- Do not eat or drink for 30 minutes after rinsing.

Other information

Do not use if safety seal is broken or missing

Inactive Ingredients

Water, Flavor, Citric Acid, Glycerin, Menthol, PEG-40 Hydrogenated Castor Oil, Sodium Benzoate, Sodium Bicarbonate, Sodium Chlorite, Sodium Hydroxide, Sucralose

PRINCIPAL DISPLAY PANEL - 473 mL Bottle Label

ANTICAVITY FLUORIDE RINSE

STRENGTHENS
TEETH

TheraBreath™
DENTIST FORMULATED
OVERNIGHT
ORAL RINSE

FIGHTS BAD BREATH FOR 12 HOURS*
HELPS PREVENT CAVITIES & REBUILD ENAMEL

No Alcohol • No Dyes
Non Burning

IMPORTANT:
Read directions
for proper use.

16 fl. oz.
473 mL

CHAMOMILE MINT